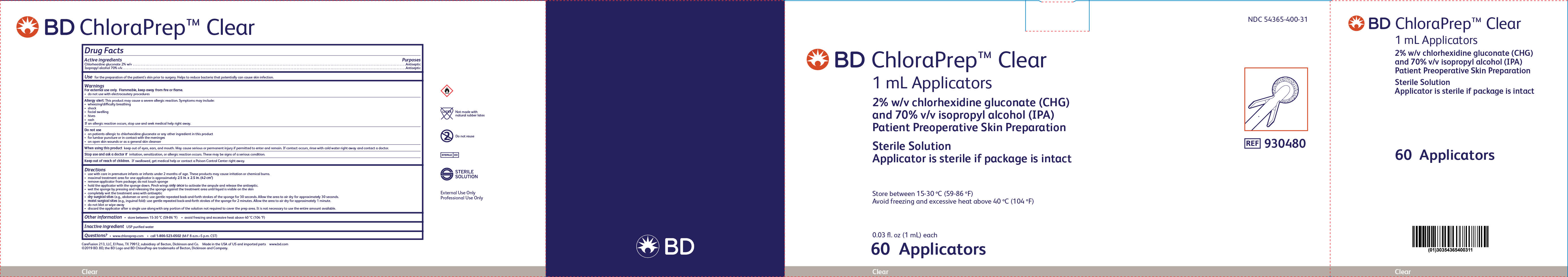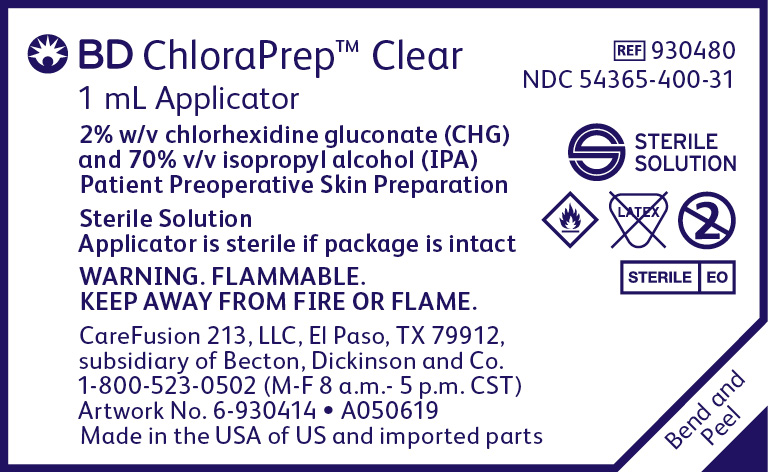 DRUG LABEL: ChloraPrep One-Step
NDC: 54365-400 | Form: SOLUTION
Manufacturer: CareFusion 213, LLC
Category: otc | Type: HUMAN OTC DRUG LABEL
Date: 20251104

ACTIVE INGREDIENTS: CHLORHEXIDINE GLUCONATE 20 mg/1 mL; ISOPROPYL ALCOHOL 0.7 mL/1 mL
INACTIVE INGREDIENTS: WATER

BD ChloraPrep™ Clear 1 mL Applicators
Sterile Solution

Active Ingredients

Chlorhexidine gluconate 2% w/v

Isopropyl alcohol 70% v/v

Purposes

Antiseptic

Antiseptic

Use

for the preparation of the patient’s skin prior to surgery. Helps to reduce bacteria that potentially can cause skin infection.

Warnings

For external use only.

Flammable, keep away from fire or flame.

• do not use with electrocautery procedures

Allergy alert:

This product may cause a severe allergic reaction. Symptoms may include:

• wheezing/difficulty breathing • shock • facial swelling • hives • rash

If an allergic reaction occurs, stop use and seek medical help right away.

Do not use

• on patients allergic to chlorhexidine gluconate or any other ingredient in this product

• for lumbar puncture or in contact with the meninges

• on open skin wounds or as a general skin cleanser

When using this product

keep out of eyes, ears, and mouth. May cause serious or permanent injury if permitted to enter and remain. If contact

occurs, rinse with cold water right away and contact a doctor.

Stop use and ask a doctor if

irritation, sensitization, or allergic reaction occurs. These may be signs of a serious condition.

Keep out of reach of children.

If swallowed, get medical help or contact a Poison Control Center right away.

Directions

- use with care in premature infants or infants under 2 months of age.These products may cause irritation or chemical burns.
- maximal treatment area for one applicator is approximately 2.5 in. x 2.5 in. (42 cm2)
- remove applicator from package; do not touch sponge
- hold the applicator with the sponge down. Pinch wings only once to activate the ampule and release the antiseptic.
- wet the sponge by pressing and releasing the sponge against the treatment area until liquid is visible on the skin
- completely wet the treatment area with antiseptic
- dry surgical sites (e.g., abdomen or arm): use gentle repeated back-and-forth strokes for approximately 30 seconds. Allow the area to air dry for approximately 30 seconds.
- moist surgical sites (e.g., inguinal fold): use gentle repeated back-and-forth strokes for approximately 2 minutes. Allow the area to air dry for approximately 1 minute.
- do not blot or wipe away
- discard the applicator after a single use along with any portion of the solution not required to cover the prep area. It is not necessary to use the entire amount available.

Other Information

• store between 15-30 °C (59-86 °F)

• avoid freezing and excessive heat above 40 °C (104 °F)

Inactive Ingredient

USP purified water

Questions?

www.chloraprep.com • call 1-800-523-0502 (M-F 8 a.m.-5 p.m. CST)

BD ChloraPrep™ 1 mL Clear Applicators Principal Display Panel-Package Label

Principal Display Panel-Package Label

BD ChloraPrep™ Clear

1 mL Applicator

2% w/v chlorhexidine gluconate (CHG)

and 70% v/v Isopropyl alcohol (IPA)

Patient Preoperative Skin Preparation

Sterile Solution

Applicator is sterile if package is intact

NDC 54365-400-31

REF 930480

BD ChloraPrep™ 1 mL Clear Applicators Principal Display Panel-Carton Label

Principal Display Panel-Carton

BD ChloraPrep™ Clear

1 mL Applicators

2% w/v chlorhexidine gluconate (CHG)

and 70% v/v Isopropyl alcohol (IPA)

Patient Preoperative Skin Preparation

Sterile Solution

Applicator is sterile if package is intact

60 Applicators

NDC 54365-400-31

REF 930480